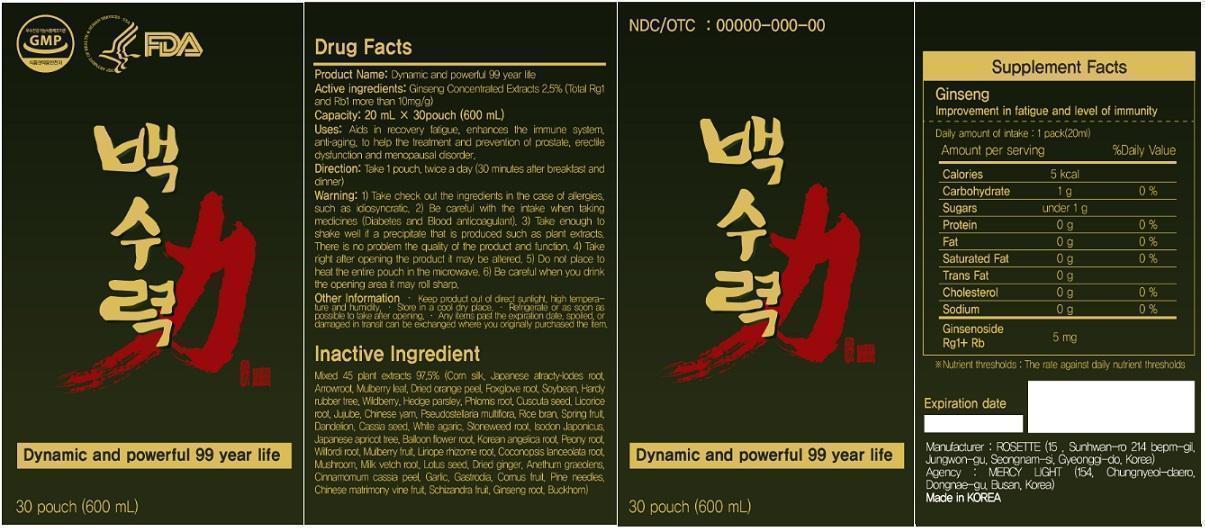 DRUG LABEL: V.S. Power / Vacsu Power (Dynamic and Powerful 99 year life)
NDC: 69568-1001 | Form: LIQUID
Manufacturer: Mercylignt
Category: otc | Type: HUMAN OTC DRUG LABEL
Date: 20150128

ACTIVE INGREDIENTS: ASIAN GINSENG 0.5 g/20 mL
INACTIVE INGREDIENTS: CORN SILK; ATRACTYLODES JAPONICA ROOT; MARANTA ARUNDINACEA ROOT; MORUS ALBA LEAF; ORANGE PEEL; DIGITALIS PURPUREA WHOLE; SOYBEAN; EUCOMMIA ULMOIDES WHOLE; RUBUS FRUTICOSUS SEED; TORILIS JAPONICA WHOLE; LEUCAS CEPHALOTES WHOLE; CUSCUTA JAPONICA SEED; LICORICE; JUJUBE FRUIT; CHINESE YAM; PSEUDOSTELLARIA HETEROPHYLLA WHOLE; RICE BRAN; TARAXACUM OFFICINALE ROOT; SENNA OBTUSIFOLIA SEED; LEUCOAGARICUS LEUCOTHITES WHOLE; LITHOSPERMUM OFFICINALE ROOT; ISODON RUBESCENS WHOLE; PRUNUS MUME WHOLE; PLATYCODON GRANDIFLORUS ROOT; OSTERICUM GROSSESERRATUM ROOT; PAEONIA LACTIFLORA ROOT; TRIPTERYGIUM WILFORDII ROOT; WHITE MULBERRY; LIRIOPE MUSCARI ROOT; CODONOPSIS LANCEOLATA ROOT; CULTIVATED MUSHROOM; ASTRAGALUS PROPINQUUS ROOT; NELUMBO NUCIFERA SEED; GINGER; ANETHUM GRAVEOLENS WHOLE; CHINESE CINNAMON; GARLIC; GASTRODIA ELATA TUBER; CORNUS OFFICINALIS FRUIT; PINE NEEDLE OIL (PINUS SYLVESTRIS); LYCIUM BARBARUM FRUIT; SCHISANDRA CHINENSIS FRUIT; GINSENOSIDES; PLANTAGO MAJOR

V.S. Power / Vacsu Power (Dynamic and Powerful 99 year life)

ACTIVE INGREDIENT

Active ingredients: Ginseng Concentrated Extracts 2.5% (Total Rg1 and Rb1 more than 10mg/g)

PURPOSE

Stimulant

Keep out of reach of children.

INDICATIONS AND USAGE

Uses: Aids in recovery fatigue, enhances the immune system, anti‐aging, to help the treatment and
prevention of prostate, erectile dysfunction and menopausal disorder.

WARNINGS

Warning: 1) Take check out the ingredients in the case of allergies, such as idiosyncratic. 2) Be careful with the intake when taking medicines (Diabetes and Blood anticoagulant). 3) Take enough to shake well if a precipitate that is produced such as plant extracts. There is no problem the quality of the product and function. 4) Take right after opening the product it may be altered. 5) Do not place to heat the entire pouch in the microwave. 6) Be careful when you drink the opening area it may roll sharp.

DOSAGE AND ADMINISTRATION

Direction: Take 1 pouch, twice a day (30 minutes after breakfast and dinner)

Other Information • Keep product out of direct sunlight, high temperature and humidity.• Store in a cool dry place. • Refrigerate or as soon as possible to take after opening. • Any items past the expiration date, spoiled, or damaged in transit can be exchanged where you originally purchased the item.

Inactive Ingredient:

Mixed 45 plant extracts 97.5% (Corn silk, Japanese atracty‐lodes root, Arrowroot, Mulberry leaf, Dried orange peel, Foxglove root, Soybean, Hardy rubber tree, Wildberry, Hedge parsley, Phlomis root, Cuscuta seed, Licorice root, Jujube, Chinese yam, Pseudostellaria multiflora, Rice bran, Spring fruit, Dandelion, Cassia seed, White agaric, Stoneweed root, Isodon Japonicus, Japanese apricot tree, Balloon flower root, Korean angelica root, Peony root, Wilfordi root, Mulberry fruit, Liriope rhizome root, Coconopsis lanceolata root, Mushroom, Milk vetch root, Lotus seed, Dried ginger, Anethum graeolens, Cinnamomum cassia peel, Garlic, Gastrodia, Cornus fruit, Pine needles, Chinese matrimony vine fruit, Schizandra fruit, Ginseng root, Buckhorn)